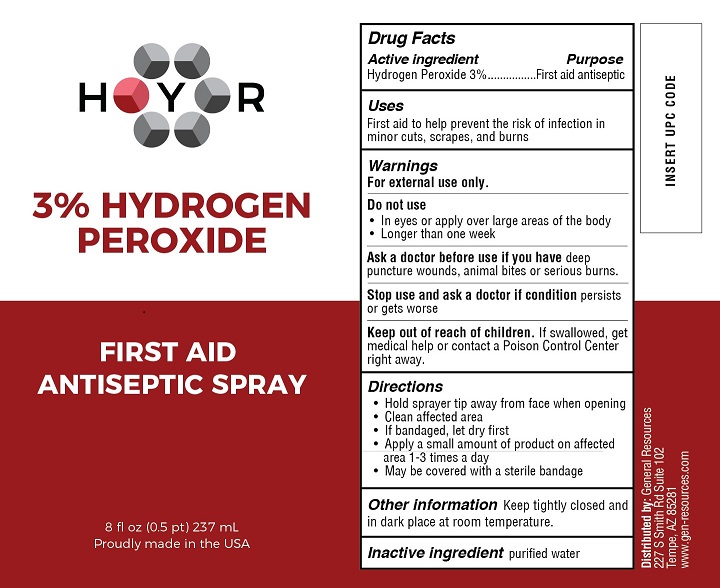 DRUG LABEL: HYR Hydrogen Peroxide
NDC: 70481-320 | Form: LIQUID
Manufacturer: General Resources LLC
Category: otc | Type: HUMAN OTC DRUG LABEL
Date: 20201015

ACTIVE INGREDIENTS: HYDROGEN PEROXIDE 3 g/100 mL
INACTIVE INGREDIENTS: WATER

HYR Hydrogen Peroxide 3%

Drug Facts

Active ingredient

Hydrogen Peroxide 3%

Purpose

First Aid Antiseptic

Uses

First aid to help prevent infection in minor cuts, scrapes, and burns

Warnings

For external use only.

Do not use

- In eyes or apply over large areas of the body
- Longer than one week

Ask a doctor before use if you have deep or puncture wounds, animal bites or serious burns.

Stop use and ask a doctor if condition persists or gets worse

Keep out of reach of children. If swallowed, get medical help or contact a Poison Control Center right away.

Directions

- Hold sprayer tip away from face when opening
- Clean the affected area
- If bandaged, let dry first
- Apply a small amount of product on affected area 1-3 times a day
- May be covered with a sterile bandage

Other information

Keep tightly closed and in a dark place at room temperature.

Inactive ingredient

purified water

Distributed by: General Resources

227 S Smith Rd Suite 102

Tempe, AZ 85281

www.gen-resources.com

PACKAGE LABEL

HYR

3% HYDROGEN PEROXIDE

FIRST AID ANTISEPTIC SPRAY

8 fl oz (0.5 pt) 237 mL

Proudly made in the USA